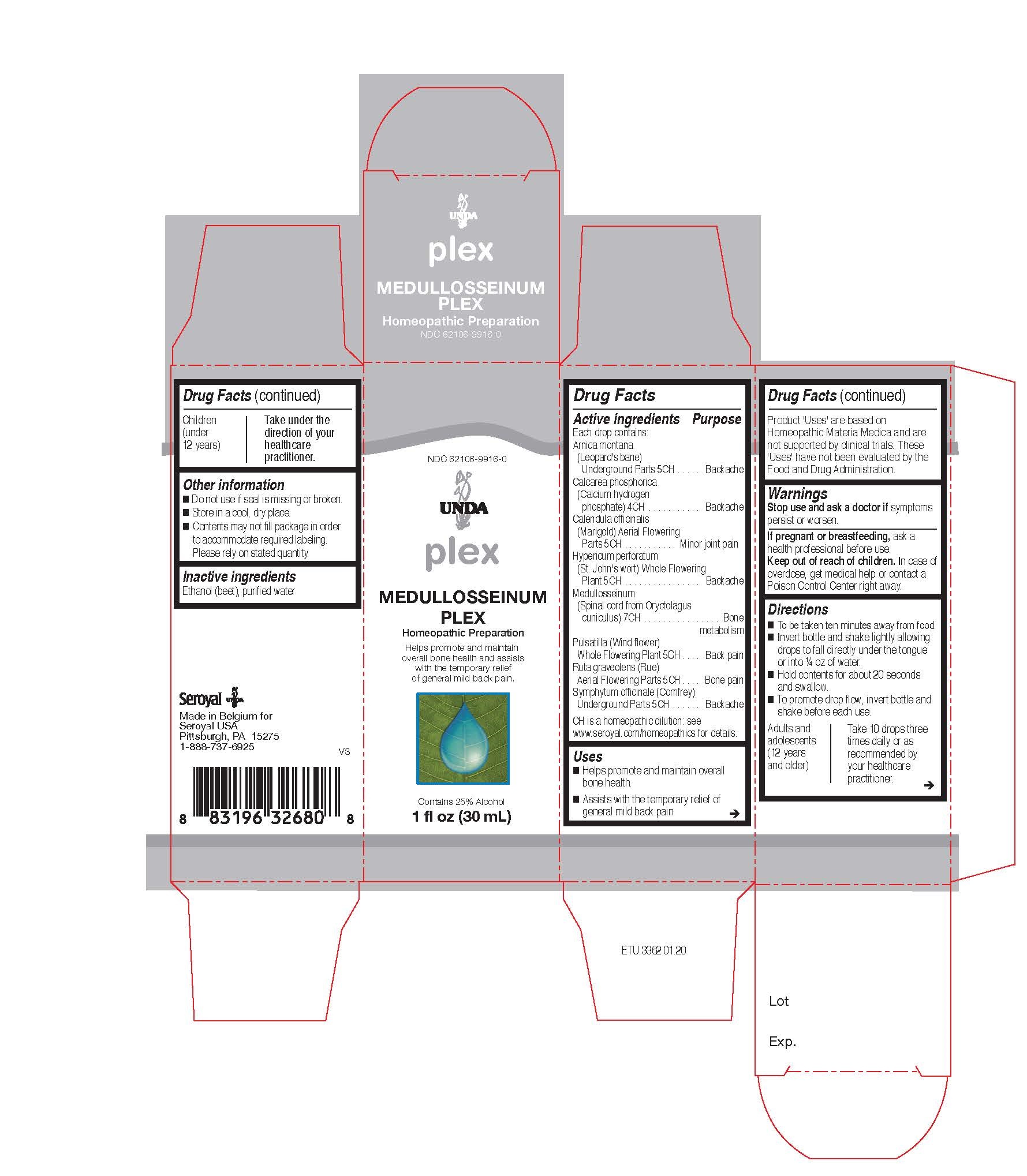 DRUG LABEL: MEDULLOSSEINUM PLEX
NDC: 62106-9916 | Form: LIQUID
Manufacturer: Seroyal USA
Category: homeopathic | Type: HUMAN OTC DRUG LABEL
Date: 20201009

ACTIVE INGREDIENTS: HYPERICUM PERFORATUM 5 [hp_C]/30 mL; ARNICA MONTANA ROOT 5 [hp_C]/30 mL; CALCIUM PHOSPHATE, DIBASIC, ANHYDROUS 4 [hp_C]/30 mL; COMFREY ROOT 5 [hp_C]/30 mL; PULSATILLA VULGARIS 5 [hp_C]/30 mL; RUTA GRAVEOLENS FLOWERING TOP 5 [hp_C]/30 mL; CALENDULA OFFICINALIS FLOWERING TOP 5 [hp_C]/30 mL; ORYCTOLAGUS CUNICULUS SPINAL CORD 7 [hp_C]/30 mL
INACTIVE INGREDIENTS: WATER; ALCOHOL

MEDULLOSSEINUM PLEX

Active ingredients

Each drop contains equal parts of:
Arnica montana (Leopard's bane) Underground Parts 5CH
Calcarea phosphorica (Calcium hydrogen phosphate) 4CH
Calendula officinalis (Marigold) Flowering Top 5CH
Hypericum perforatum (St. John's wort) Whole Plant 5CH
Medullosseinum (Spinal cord from Oryctolagus cuniculus) 7CH
Pulsatilla (Wind flower) Whole Flowering Plant 5CH
Ruta graveolens (Rue) Aerial Parts 5CH
Symphytum officinale (Comfrey) Underground Parts 5CH

Uses

Helps promote and maintain overall bone health.

Assists with the temporary relief of general mild back pain.

Warnings
Stop use and ask a doctor if symptoms persist or worsen.

If pregnant or breastfeeding, ask a health professional before use.
Keep out of reach of children.

In case of overdose, get medical help or contact a Poison Control Center right away.

Stop use and ask a doctor if symptoms persist or worsen.

PREGNANCY OR BREAST FEEDING

If pregnant or breastfeeding, ask a health professional before use.

Keep out of reach of children.

OVERDOSAGE

In case of overdose, get medical help or contact a Poison Control Center right away.

Other information
Do not use if seal is missing or broken.
Store in a cool, dry place.

Contents may not fill package in order to accommodate required labeling. Please rely on stated quantity.

Inactive ingredients
Ethanol (beet), purified water

Directions
To be taken ten minutes away from food.
Invert bottle and shake lightly allowing drops to fall directly under the tongue or into ¼ oz of water.
Hold contents for about 20 seconds and swallow.
To promote drop flow, invert bottle and shake before each use.

Adults and adolescents (12 years and older)

Take 10 drops three times daily or as recommended by your healthcare practitioner.

Children (under 12 years)

Take under the direction of your healthcare practitioner.

Uses

Helps promote and maintain overall bone health.
Assists with the temporary relief of general mild back pain.

Directions

To be taken ten minutes away from food.
Invert bottle and shake lightly allowing drops to fall directly under the tongue or into ¼ oz of water.
Hold contents for about 20 seconds and swallow.
To promote drop flow, invert bottle and shake before each use.

Adults and adolescents (12 years and older)

Take 10 drops three times daily or as recommended by your healthcare practitioner.

Children (under 12 years)

Take under the direction of your healthcare practitioner.

PACKAGE LABEL

NDC 62106-9916-0

UNDA

Plex

MEDULLOSSEINUM PLEX

Homeopathic Preparation

For the temporary relief of general mild back pain.

Contains 25% Alcohol
1 fl oz (30 mL)